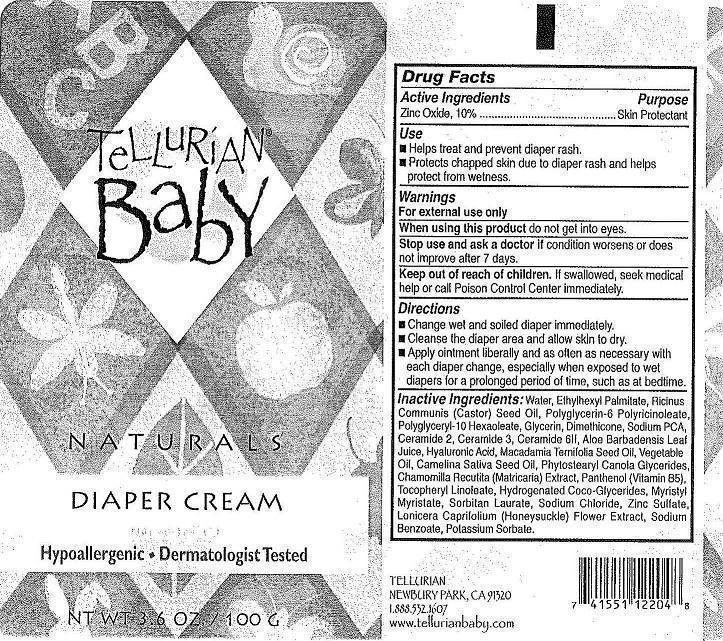 DRUG LABEL: BABY DIAPER
NDC: 42643-101 | Form: CREAM
Manufacturer: TELLURIAN
Category: otc | Type: HUMAN OTC DRUG LABEL
Date: 20141115

ACTIVE INGREDIENTS: ZINC OXIDE 10 g/10 g
INACTIVE INGREDIENTS: WATER; ETHYLHEXYL PALMITATE; CASTOR OIL; POLYGLYCERIN-6; POLYGLYCERYL-10 HEXAOLEATE; GLYCERIN; DIMETHICONE; SODIUM PYRROLIDONE CARBOXYLATE; CERAMIDE 3; CERAMIDE 6 II; CERAMIDE 2; ALOE VERA LEAF; HYALURONIC ACID; MACADAMIA OIL; CORN OIL; CANOLA OIL; MATRICARIA CHAMOMILLA WHOLE; PANTHENOL; .ALPHA.-TOCOPHEROL ACETATE; Coco-Glycerides; MYRISTYL MYRISTATE; SORBITAN MONOLAURATE; SODIUM CHLORIDE; ZINC SULFATE ANHYDROUS; POTASSIUM SORBATE; LONICERA CAPRIFOLIUM FLOWER; SODIUM BENZOATE

ACTIVE INGREDIENTS

ZINC OXIDE, 10%

PURPOSE

SKIN PROTECTANT

USE

- HELPS TREAT AND PREVENT DIAPER RASH.
- PROTECTS CHAPPED SKIN DUE TO DIAPER RASH AND HELPS PROTECT FROM WETNESS.

WARNINGS

FOR EXTERNAL USE ONLY

WHEN USING THIS PRODUCT DO NOT GET INTO EYES.

STOP USE AND ASK A DOCTOR IF CONDITION WORSENS OR DOES NOT IMPROVE AFTER 7 DAYS.

KEEP OUT OF REACH OF CHILDREN. IF SWALLOWED, SEEK MEDICAL HELP OR CALL POISON CONTROL CENTER IMMEDIATELY.

DIRECTIONS

- CHANGE WET AND SOILED DIAPER IMMEDIATELY
- CLEANSE THE DIAPER AREA AND ALLOW SKIN TO DRY.
- APPLY OINTMENT LIBERALLY AND AS OFTEN AS NECESSARY WITH EACH DIAPER CHANGE, ESPECIALLY WHEN EXPOSED TO WET DIAPERS FOR A PROLONGED PERIOD OF TIME, SUCH AS BEDTIME.

INACTIVE INGREDIENT

Inactive Ingredients: Water, Ethylhexyl Palmitate, Ricinus Communis (Castor) Seed Oil, Polyglycerin-6 Polyricinoleate, Polyglyceryl-10 Hexaoleate, Glycerin, Dimethicone, Sodium PCA, Ceramide 2, Ceramide 3, Ceramide 6lf, Aloe Barbadensis Leaf Juice, Hyaluronic Acid, Macadamia Ternifolia Seed Oil, Vegetable Oil, Camellia Saliva Seed Oil, Phytostearyl Canola Glycerides, Chamomilla Recutita (Matricaria) Extract, Panthenol (Vitamin B5), Tocopheryl Linoleate, Hydrogenated Coco-Glycerides, Myristyl Myristate, Sorbitan Laurate, Sodium Chloride, Zinc Sulfate, Lonicera Caprifolium (Honeysuckle) Flower Extract, Sodium Benzoate, Potassium Sorbate.